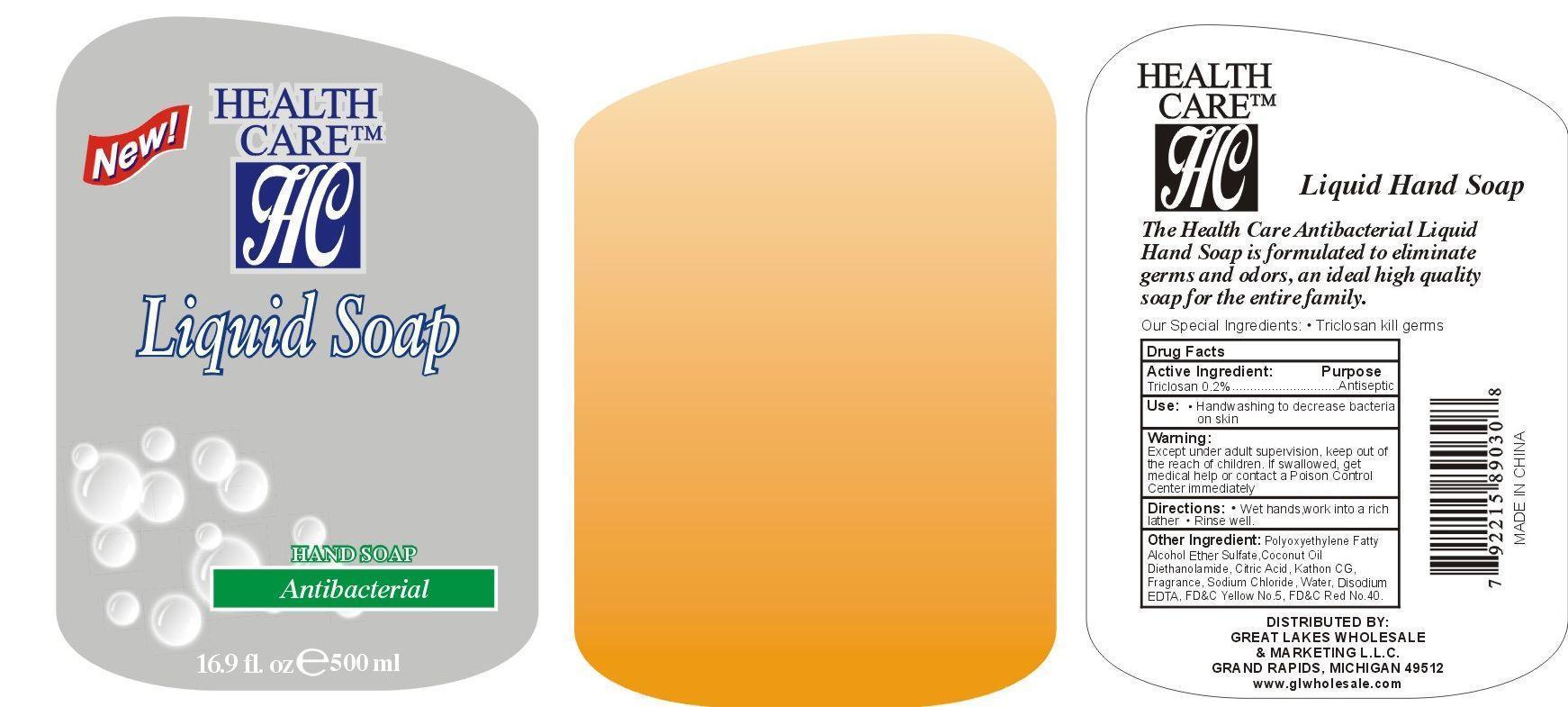 DRUG LABEL: Liquid Hand Cleanse
NDC: 57337-016 | Form: GEL
Manufacturer: Rejoice International, Inc.
Category: otc | Type: HUMAN OTC DRUG LABEL
Date: 20240228

ACTIVE INGREDIENTS: TRICLOSAN 10 mg/500 mg
INACTIVE INGREDIENTS: CETETH-7; ETHYL SULFATE; COCONUT OIL; DIETHANOLAMINE; CITRIC ACID MONOHYDRATE; OCTHILINONE; WATER; SODIUM CHLORIDE; EDETATE DISODIUM; FD&C YELLOW NO. 5; FD&C RED NO. 40

Liquid Hand Cleanse

Active Ingredient Purpose

Triclosan 0.2%......................Antiseptic

PURPOSE

Health Care Instant Hand Sanitizer - Ice Clear - Extra Enriched with Vitamin E Bead & Aloe

Kills 99.9% of Germs without water or towels!

Keep out of reach of children. If swallowed, get medical help or contact a Poison Control Center right away.

USE:

- handwashing to decrease bacteria on the skin

Warnings:

for external use only.

Flammable. Keep away from heat and flame.

Do not use in the eyes. In case of contact, rinse eyes thoroughly with water.

Stop use and ask a doctor if irritation and redness develop and persist for more than 72 hours.

Directions:

- wet hands thoroughly with product
- briskly rub hands together until dry
- supervise children in the use of this product

Inactive ingredients:

aloe vera leaf juice, carbomer, glycerin, propylene glycol, tocopheryl acetate (vitamin E), triethanolamine, water.